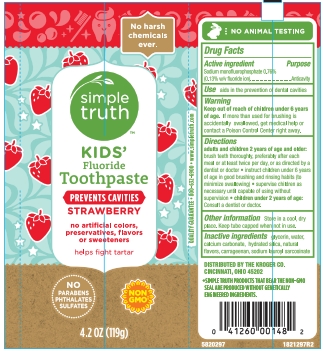 DRUG LABEL: Simple Truth
NDC: 30142-146 | Form: PASTE, DENTIFRICE
Manufacturer: Kroger Company
Category: otc | Type: HUMAN OTC DRUG LABEL
Date: 20251215

ACTIVE INGREDIENTS: SODIUM MONOFLUOROPHOSPHATE 0.76 g/100 g
INACTIVE INGREDIENTS: GLYCERIN; CARRAGEENAN; CALCIUM CARBONATE; HYDRATED SILICA; WATER; SODIUM LAUROYL SARCOSINATE

5820028 Kroger Kids Fluoride Toothpaste Strawberry

Drug Facts

Active ingredient

Sodium monofluorophosphate 0.76% (0.13% w/v fluoride ion)

Purpose

Anticavity

Use

Helps protect against cavities

Warnings

Keep out of reach of children under 6 years of age. If more than used for brushing is accidentally swallowed, get medical help or contact a Poison Control Center right away.

Directions

Adults and children 2 years of age and older: brush teeth thorughly preferably after each meal or at least twice a day, or as directed by a dentist or doctor.

Children 2 to 6 years: use a pea-sized amount and supervise child's brushing and rinsing (to minimize swallowing).

Children under 2 years of age: consult a dentist or physician.

INACTIVE INGREDIENT

Inactive ingredients Glycerin, Water, Calcium Carbonate, Hydrated Silica, Natural Flavor, Carrageenan, Sodium Lauroyl Sarcosinate

Other information

Store in a cool dry place. Keep tube covered when not in use.

DISTRIBUTED BY THE KROGER CO.

CINCINNATI, OHIO 45202

PACKAGE LABEL

simple truth

KIDS' Fluoride Toothpaste

PREVENTS CAVITIES

STRAWBERRY

no artificial colors, preservatives, flavors or sweeteners

4.2 OZ (119g)